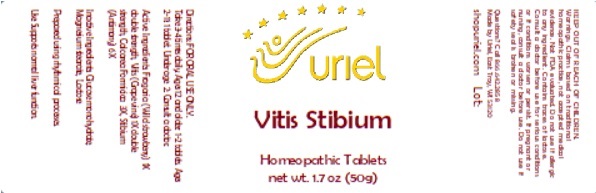 DRUG LABEL: Vitis Stibium
NDC: 48951-9377 | Form: TABLET
Manufacturer: Uriel Pharmacy, Inc.
Category: homeopathic | Type: HUMAN OTC DRUG LABEL
Date: 20241113

ACTIVE INGREDIENTS: FRAGARIA VESCA WHOLE 1 [hp_X]/1 1; VITIS VINIFERA LEAF 1 [hp_X]/1 1; CALCIUM FORMATE 3 [hp_X]/1 1; ANTIMONY 6 [hp_X]/1 1
INACTIVE INGREDIENTS: LACTOSE, UNSPECIFIED FORM; MAGNESIUM STEARATE; DEXTRATES

Vitis Stibium

INDICATIONS AND USAGE

Directions: FOR ORAL USE ONLY.

DOSAGE AND ADMINISTRATION

Take 3-4 times daily. Ages 12 and older: 1-2 tablets. Ages 2-11: 1 tablet. Under age 2: Consult a doctor.

ACTIVE INGREDIENT

Active Ingredients: Fragaria (Wild strawberry) 1X double strength, Vitis (Grape vine) 1X double strength, Calcarea Formicica 3X, Stibium (Antimony) 6X

Inactive Ingredients: Glucose monohydrate, Magnesium stearate, Lactose

Prepared using rhythmical processes.

PURPOSE

Use: Supports normal liver function.

KEEP OUT OF REACH OF CHILDREN.

WARNINGS

Warnings: Claims based on traditional homeopathic practice, not accepted medical evidence. Not FDA evaluated. Do not use if allergic to any ingredient. Contains traces of lactose. Consult a doctor before use for serious conditions or if conditions worsen or persist. If pregnant or nursing, consult a doctor before use. Do not use if safety seal is broken or missing.

Questions? Call 866.642.2858
Made by Uriel, East Troy, WI 53120
shopuriel.com Lot: